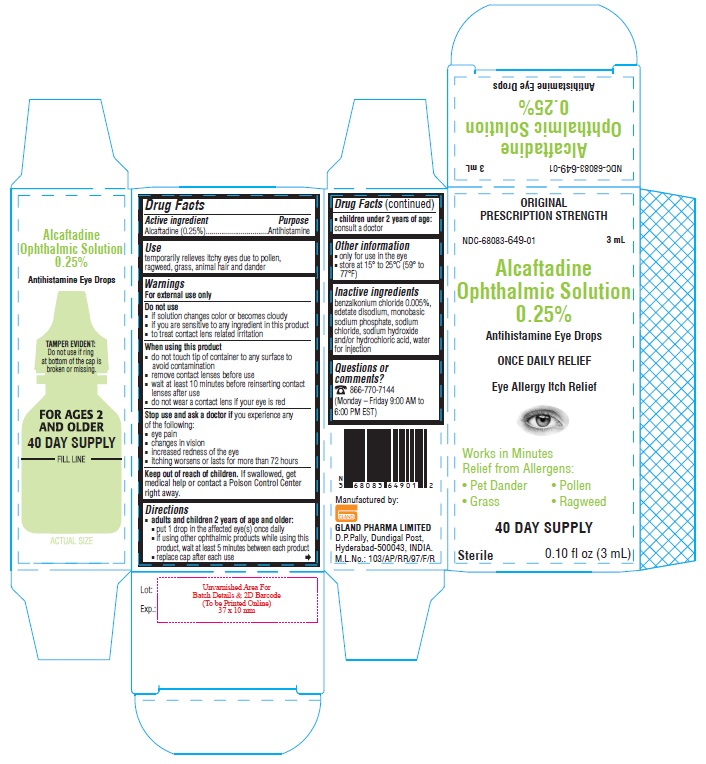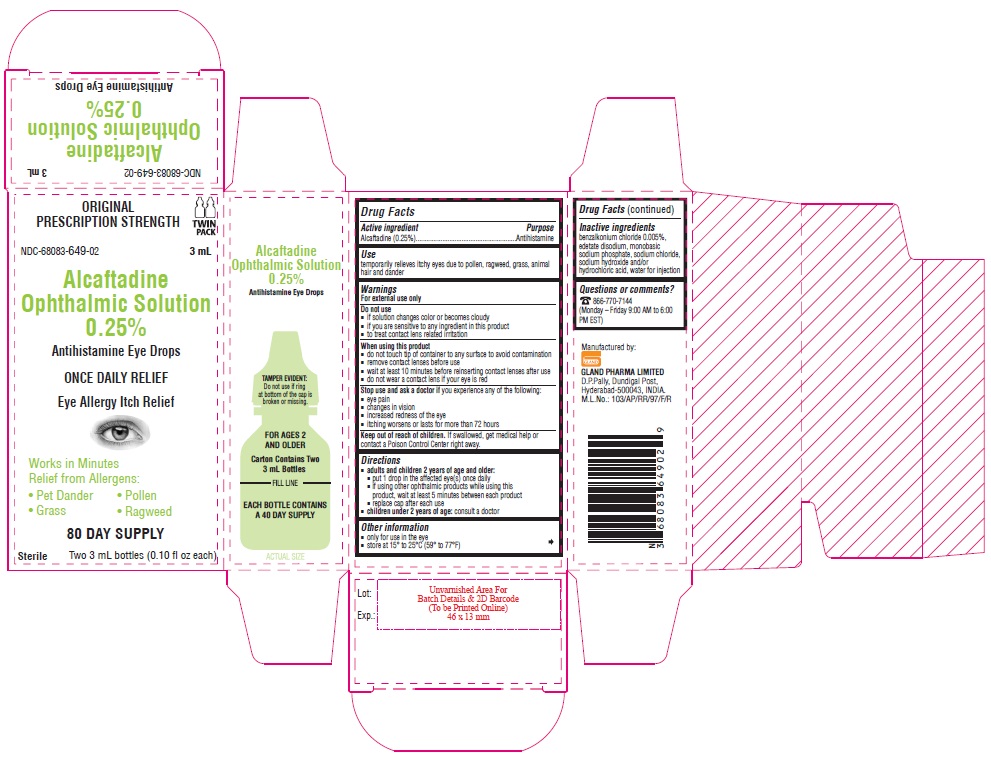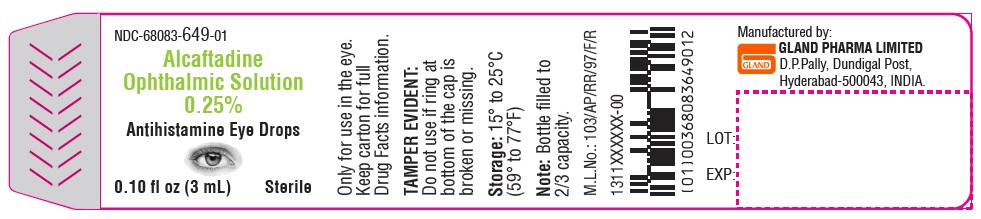 DRUG LABEL: Alcaftadine
NDC: 68083-649 | Form: SOLUTION/ DROPS
Manufacturer: Gland Pharma Limited
Category: otc | Type: Human OTC Drug Label
Date: 20240305

ACTIVE INGREDIENTS: ALCAFTADINE 2.5 mg/1 mL
INACTIVE INGREDIENTS: BENZALKONIUM CHLORIDE; EDETATE DISODIUM; HYDROCHLORIC ACID; SODIUM PHOSPHATE, MONOBASIC; SODIUM CHLORIDE; SODIUM HYDROXIDE; WATER

Alcaftadine Ophthalmic Solution 0.25%

Active ingredient

Alcaftadine 0.25%

Purpose

Antihistamine

Use

temporarily relieves itchy eyes due to pollen, ragweed, grass, animal hair and dander

Warnings

For external use only

Do not use

■ if solution changes color or becomes cloudy
■ if you are sensitive to any ingredient in this product
■ to treat contact lens related irritation

When using this product

■ do not touch tip of container to any surface to avoid contamination
■ remove contact lenses before use
■ wait at least 10 minutes before reinserting contact lenses after use
■ do not wear a contact lens if your eye is red

Stop use and ask a doctor if

you experience any of the following:
■ eye pain
■ changes in vision
■ increased redness of the eye
■ itching that worsens or lasts for more than 72 hours

Keep out of reach of children

If swallowed, get medical help or contact a Poison Control Center right away.

Directions

- adults and children 2 years of age and older:
  - put 1 drop in the affected eye(s) once daily
  - if using other ophthalmic products while using this product, wait at least 5 minutes between each product
  - replace cap after each use
- children under 2 years of age: consult a doctor

Other information

- only for use in the eye
- store at 15° to 25°C (59° to 77°F)

Inactive ingredients

benzalkonium chloride 0.005%, edetate disodium, monobasic sodium phosphate, sodium chloride, sodium hydroxide and/or hydrochloric acid, water for injection

Questions or comments?

866-770-7144

(Monday – Friday 9:00 AM to 6:00 PM EST)

PACKAGE LABEL-PRINCIPAL DISPLAY PANEL

Container Label - 0.25% (3 mL)

NDC-68083-649-01
Alcaftadine
Ophthalmic Solution
0.25%
Antihistamine Eye Drops
0.10 fl oz (3 mL) Sterile

Container Carton - 0.25% (3 mL)

ORIGINAL PRESCRIPTION STRENGTH
NDC-68083-649-01 3 mL
Alcaftadine
Ophthalmic Solution
0.25%
Antihistamine Eye Drops
ONCE DAILY RELIEF
Eye Allergy Itch Relief

Works in Minutes
Relief from Allergens:
• Pet Dander • Pollen
• Grass • Ragweed
40 DAY SUPPLY

Sterile 0.10 fl oz (3 mL)

Container Carton - 0.25% (3 mL) - Twin Pack

ORIGINAL PRESCRIPTION STRENGTH

TWIN PACK
NDC-68083-649-02 3 mL
Alcaftadine
Ophthalmic Solution
0.25%
Antihistamine Eye Drops
ONCE DAILY RELIEF
Eye Allergy Itch Relief
Works in Minutes
Relief from Allergens:
• Pet Dander • Pollen
• Grass • Ragweed
80 DAY SUPPLY
Sterile Two 3 mL bottles (0.10 fl oz each)